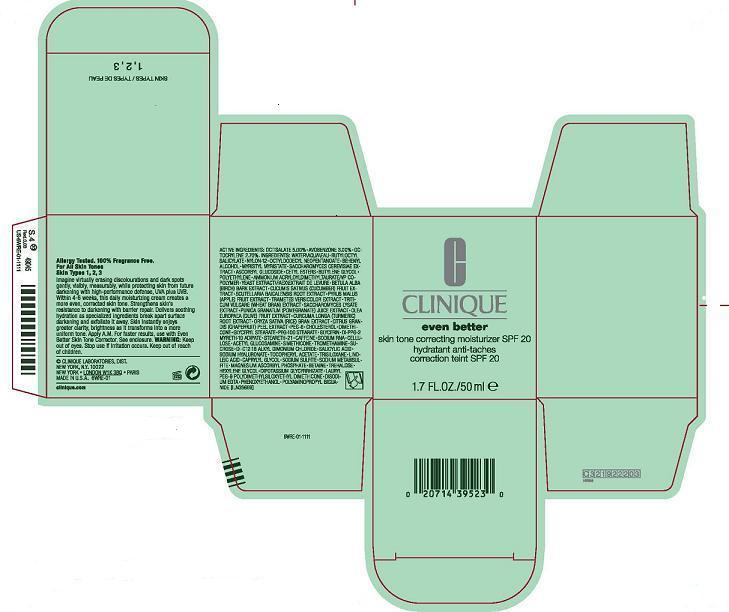 DRUG LABEL: EVEN BETTER SKIN TONE CORRECTING MOSTURIZER
NDC: 49527-759 | Form: CREAM
Manufacturer: CLINIQUE LABORATORIES, INC.
Category: otc | Type: HUMAN OTC DRUG LABEL
Date: 20100518

ACTIVE INGREDIENTS: OCTISALATE 5.0 mL/100 mL; AVOBENZONE 3.0 mL/100 mL; OCTOCRYLENE 2.7 mL/100 mL

ACTIVE INGREDIENT

ACTIVE INGREDIENTS: octisalate 5.00% [] avobenzone 3.00% [] octocrylene 2.70%

WHEN USING

DIRECTIONS: Apply A.M.

WARNINGS

WARNING: Keep out of eyes. Stop use if irritation occurs. Keep out of reach of children.

PACKAGE LABEL

PRINCIPAL DISPLAY PANEL:

CLINIQUE

even better

Skin tone correcting moisturizer SPF 20

1.7 FL.OZ./50 ml

CLINIQUE LABORATORIES, DIST.

NEW YORK, N.Y. 10022